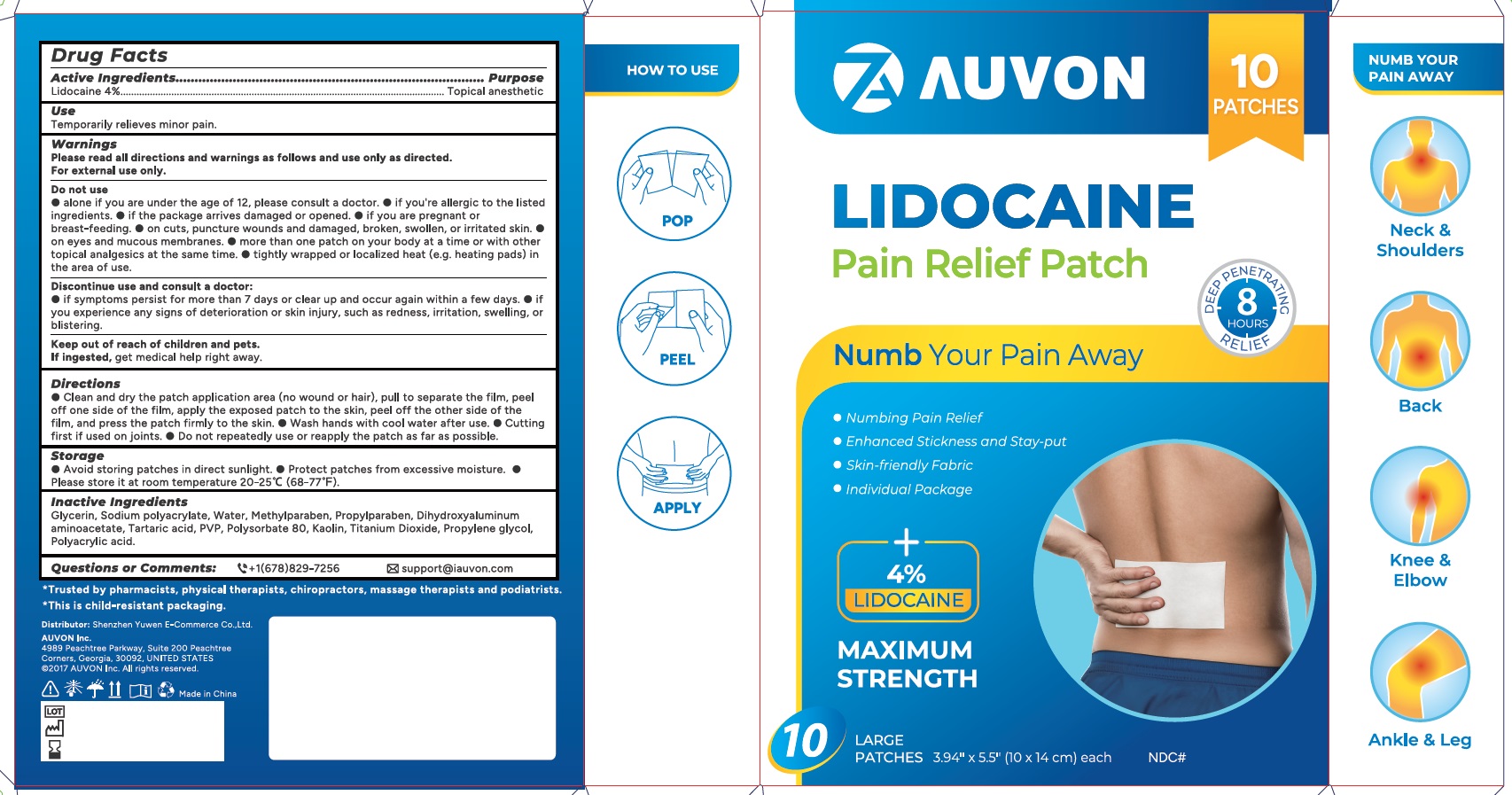 DRUG LABEL: AUVON Pain Relief
NDC: 83391-005 | Form: PATCH
Manufacturer: SHENZHEN YUWEN E-COMMERCE CO., LTD.
Category: otc | Type: HUMAN OTC DRUG LABEL
Date: 20241208

ACTIVE INGREDIENTS: LIDOCAINE HYDROCHLORIDE 360 mg/1 1
INACTIVE INGREDIENTS: GLYCERIN; WATER; SODIUM POLYACRYLATE (8000 MW); METHYLPARABEN; PROPYLPARABEN; DIHYDROXYALUMINUM AMINOACETATE; TARTARIC ACID; POVIDONE, UNSPECIFIED; POLYSORBATE 80; TITANIUM DIOXIDE; PROPYLENE GLYCOL; POLYACRYLIC ACID (8000 MW)

83391-005 Lidocain Pain Relief Patch

AUVON Lidocaine Pain Relief Patch

Drug Facts

Active ingredients

Lidocaine HCl 4%

Purposes

Topical Analgestic

Use

Temporarily relieves minor pain

Warnings

Please read all directions and warnings as follows and use only as directed. For external use only

Do not use

- Alone if you are under 12 years of age, please consult a doctor
- If you are allergic to the listed ingredients
- If the package arrives damaged or opened.
- If you are pregnent or breast feeding
- On cuts, puncture wounds, and damaged, broken, swollen, or irritated skin
- On eyes and mucous membranes
- More than one patch on your body at a time or with other topical analgesics at the same time
- Tightly wrapped or localized heat (e.g. heating pads) in the area of use.

Discontinue use and consult a doctor

- if symptoms persist for more than 7 days or clear up and occur again within a few days
- If you experience any signs of deterioration or skin injury, such as redness, irritation, swelling, or blistering

Keep outof reach of children and pets.

If ingested, get medical help right away.

Directions

- Clean and dry the patch application area (no wound or hair), pull to separate the film, peel off one side of the film, apply the exposed patch to the skin, peel off the other side of the film, and press the patch firmly to the skin.
- Wash hands with cool water after use
- Cutting first if used on joints
- Do not repeatedly use or reapply the patch as far as possible

Storage

- Avoid storing patches in direct sunlight
- Protect patches from excessive moisture
- Please store it at room temperature 20-25 C (68-77F)

Inactive ingredients

Glycerin, Sodium polyacrylate, Water, Methylparaben, Propylparaben, Dihydroxyaluminum aminoacetate, Tartaric acid, PVP, Polysorbate 80, Kaolin, Titanium Dioxide, Propylene glycol, Polyacrylic acid